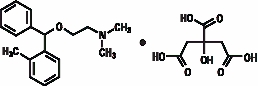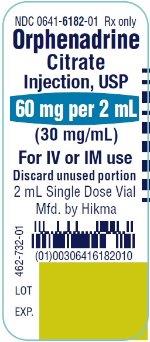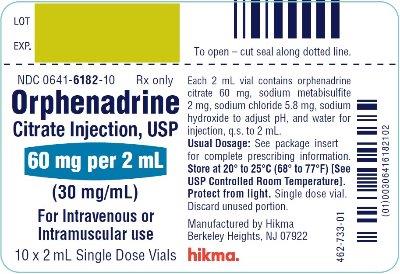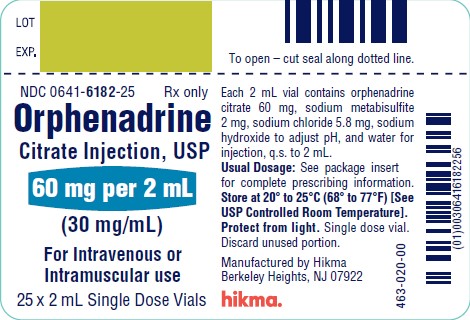 DRUG LABEL: Orphenadrine citrate
NDC: 0641-6182 | Form: INJECTION
Manufacturer: Hikma Pharmaceuticals USA Inc.
Category: prescription | Type: HUMAN PRESCRIPTION DRUG LABEL
Date: 20240808

ACTIVE INGREDIENTS: ORPHENADRINE CITRATE 60 mg/2 mL
INACTIVE INGREDIENTS: SODIUM CHLORIDE 5.8 mg/2 mL; SODIUM HYDROXIDE; SODIUM METABISULFITE 2 mg/2 mL; WATER

ORPHENADRINE CITRATE
INJECTION, USP

Rx only

DESCRIPTION

Orphenadrine citrate is the citrate salt of orphenadrine (±)-N,N-dimethyl-2-[(o-methyl-α-phenylbenzyl)oxy]-ethylamine citrate (1:1). It occurs as a white, crystalline powder having a bitter taste. It is practically odorless; sparingly soluble in water, slightly soluble in alcohol.

Each vial contains 60 mg of orphenadrine citrate in aqueous solution. Each vial also contains: sodium metabisulfite, 2 mg; sodium chloride, 5.8 mg; sodium hydroxide, to adjust pH; and water for injection, q.s. to 2 mL. The structural formula is:

C18H23NO•C6H8O7 MW 461.50

CLINICAL PHARMACOLOGY

The mode of therapeutic action has not been clearly identified, but may be related to its analgesic properties. Orphenadrine citrate does not directly relax tense muscles in man. Orphenadrine citrate also possesses anticholinergic actions.

INDICATIONS AND USAGE

Orphenadrine citrate is indicated as an adjunct to rest, physical therapy, and other measures for the relief of discomfort associated with acute painful musculoskeletal conditions.

CONTRAINDICATIONS

Contraindicated in patients with glaucoma, pyloric or duodenal obstruction, stenosing peptic ulcers, prostatic hypertrophy or obstruction of the bladder neck, cardio-spasm (megaesophagus) and myasthenia gravis.

Contraindicated in patients who have demonstrated a previous hypersensitivity to the drug.

WARNINGS

Some patients may experience transient episodes of light-headedness, dizziness or syncope. Orphenadrine citrate may impair the ability of the patient to engage in potentially hazardous activities such as operating machinery or driving a motor vehicle; ambulatory patients should therefore be cautioned accordingly.

Orphenadrine citrate injection contains sodium metabisulfite, a sulfite that may cause allergic-type reactions including anaphylactic symptoms and life-threatening or less severe asthmatic episodes in certain susceptible people. The overall prevalence of sulfite sensitivity in the general population is unknown and probably low. Sulfite sensitivity is seen more frequently in asthmatic than nonasthmatic people.

PRECAUTIONS

Confusion, anxiety and tremors have been reported in few patients receiving propoxyphene and orphenadrine concomitantly. As these symptoms may be simply due to an additive effect, reduction of dosage and/or discontinuation of one or both agents is recommended in such cases.

Orphenadrine citrate should be used with caution in patients with tachycardia, cardiac decompensation, coronary insufficiency, cardiac arrhythmias.

Safety of continuous long-term therapy with orphenadrine has not been established. Therefore, if orphenadrine is prescribed for prolonged use, periodic monitoring of blood, urine and liver function values is recommended.

Pregnancy

Teratogenic Effects

Pregnancy Category C
Animal reproduction studies have not been conducted with orphenadrine. It is also not known whether orphenadrine can cause fetal harm when administered to a pregnant woman or can affect reproduction capacity. Orphenadrine should be given to a pregnant woman only if clearly needed.

Pediatric Use

Safety and effectiveness in children have not been established; therefore, this drug is not recommended for use in the pediatric age group.

ADVERSE REACTIONS

Adverse reactions of orphenadrine are mainly due to the mild anticholinergic action of orphenadrine, and are usually associated with higher dosage. Dryness of the mouth is usually the first adverse effect to appear. When the daily dose is increased, possible adverse effects include: tachycardia, palpitation, urinary hesitancy or retention, blurred vision, dilatation of pupils, increased ocular tension, weakness, nausea, vomiting, headache, dizziness, constipation, drowsiness, hypersensitivity reactions, pruritus, hallucinations, agitation, tremor, gastric irritation, and rarely urticaria and other dermatoses. Infrequently, an elderly patient may experience some degree of mental confusion. These adverse reactions can usually be eliminated by reduction in dosage. Very rare cases of aplastic anemia associated with the use of orphenadrine tablets have been reported. No causal relationship has been established.

Rare instances of anaphylactic reaction have been reported associated with the intramuscular injection of orphenadrine citrate.

DRUG ABUSE AND DEPENDENCE

Orphenadrine has been chronically abused for its euphoric effects. The mood elevating effects may occur at therapeutic doses of orphenadrine.

OVERDOSAGE

Orphenadrine is toxic when overdosed and typically induces anticholinergic effects. In a review of orphenadrine toxicity, the minimum lethal dose was found to be 2 to 3 grams for adults; however, the range of toxicity is variable and unpredictable. Treatment for orphenadrine overdose is evacuation of stomach contents (when necessary), charcoal at repeated doses, intensive monitoring, and appropriate supportive treatment of any emergent anticholinergic effects.

DOSAGE AND ADMINISTRATION

Adults - One 2 mL vial (60 mg) intravenously or intramuscularly; may be repeated every 12 hours. Relief may be maintained by one (100 mg) orphenadrine citrate tablet twice daily.

Parenteral drug products should be inspected visually for particulate matter, whenever solution and container permit.

HOW SUPPLIED

Orphenadrine Citrate Injection, USP is supplied as follows:

Cartons of 10 (NDC 0641-6182-10) 2 mL vials, each vial containing 60 mg of orphenadrine citrate in aqueous solution.

Cartons of 25 (NDC 0641-6182-25) 2 mL vials, each vial containing 60 mg of orphenadrine citrate in aqueous solution.

Storage

Store at 20° to 25°C (68° to 77°F) [See USP Controlled Room Temperature].

Protect from light.

Single dose vial. Discard unused portion.

To report SUSPECTED ADVERSE REACTIONS, contact Hikma Pharmaceuticals USA Inc. at 1-877-845-0689, or the FDA at 1-800-FDA-1088 or www.fda.gov/medwatch.

For Product Inquiry call 1-877-845-0689.

Manufactured by:
Hikma Pharmaceuticals USA Inc.
Berkeley Heights, NJ 07922

Revised May 2023

462-734-02

PRINCIPAL DISPLAY PANEL - CONTAINER

NDC 0641-6182-01 Rx only
Orphenadrine
Citrate
Injection, USP
60 mg per 2 mL
(30 mg/mL)
For IV or IM use
Discard unused portion
2 mL Single Dose Vial

PRINCIPAL DISPLAY PANEL -SHELF PACK

NDC 0641-6182-10 Rx only
Orphenadrine
Citrate Injection, USP
60 mg per 2 mL
(30 mg/mL)
For Intravenous or
Intramuscular use
10 x 2 mL Single Dose Vials

NDC 0641-6182-25 Rx only
Orphenadrine
Citrate Injection, USP
60 mg per 2 mL
(30 mg/mL)
For Intravenous or
Intramuscular use
25 x 2 mL Single Dose Vials